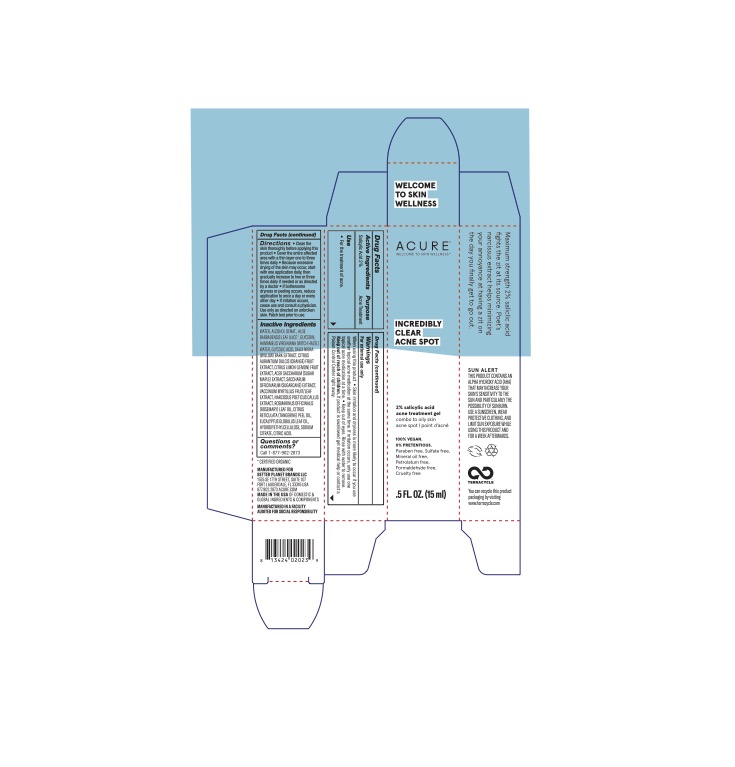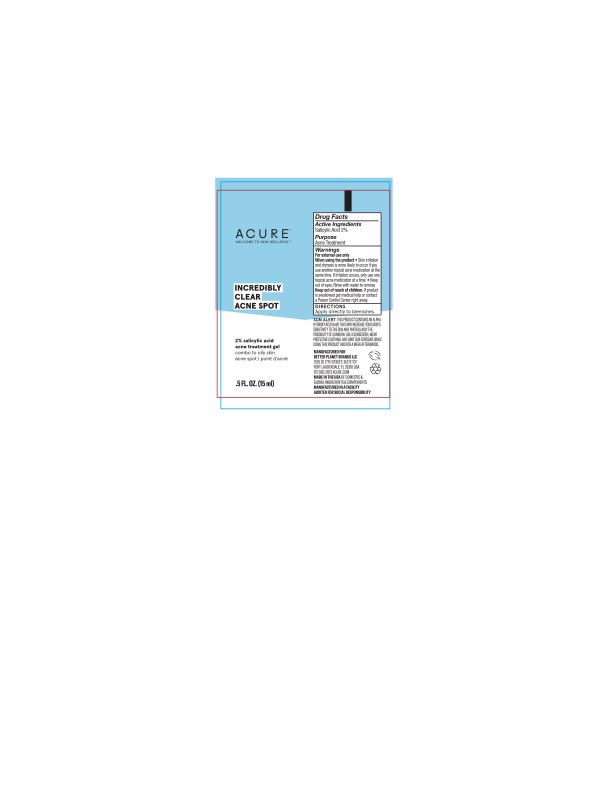 DRUG LABEL: Incredibly Clear Acne Spot
NDC: 54136-118 | Form: GEL
Manufacturer: Better Planet Brands LLC
Category: otc | Type: HUMAN OTC DRUG LABEL
Date: 20240722

ACTIVE INGREDIENTS: SALICYLIC ACID 2 g/100 g
INACTIVE INGREDIENTS: ALCOHOL; SALIX NIGRA BARK; VACCINIUM MYRTILLUS FRUITING TOP; MANDARIN OIL; WATER; CITRIC ACID MONOHYDRATE; GLYCERIN; SUGARCANE; ORANGE; ALOE VERA LEAF; ACER SACCHARUM BARK/SAP; HYDROXYETHYL CELLULOSE (4000 MPA.S AT 1%); GLYCOLIC ACID; EUCALYPTUS OIL; SODIUM CITRATE; LEMON; HAMAMELIS VIRGINIANA LEAF WATER; ROSEMARY OIL; NARCISSUS POETICUS FLOWER OIL

Incredibly Clear Acne Spot

Active Ingredients

Active ingredients Purpose

Salicylic Acid 2.0%..................... Acne Treatment

Purpose

Acne Treatment

Uses

* For the treatment of acne.

Warnings

For external use only.

WHEN USING

When using the product * Skin irritation and dryness is more likely to occur if you use another topical acne medication at the same time. If irritation occurs, only use one topical acne medication at a time. * Keep out of eyes. Rinse with water to remove.

Keep out of reach of children. If the product is swallowed get medical help or contact a Poison Control Center right away.

Directions

Directions * Clean the skin before applying this product * Cover the entire affected area with a thin layer one to three times daily * Because excessive drying of the skin may occur, start with one application daily, then gradually increase to two or three times daily if needed or as directed by a doctor * If bothersome dryness or peeling occurs, reduce applications to once a day or every other day * If irritation occurs, cease use and consult a physician. Use only as directed on unbroken skin. Patch test prior to use.

Inactive Ingredients

WATER, ALCOHOL DENAT., ALOE BARBADENSIS LEAF JUICE*, GLYCERIN, HAMAMELIS VIRGINIANA (WITCH HAZEL) WATER, GLYCOLIC ACID, SALIX NIGRA (WILLOW) BARK EXTRACT, CITRUS AURANTIUM DULCIS (ORANGE) FRUIT EXTRACT, CITRUS LIMON (LEMON) FRUIT EXTRACT, ACER SACCHARUM (SUGAR MAPLE) EXTRACT, SACCHARUM OFFICINARUM (SUGARCANE) EXTRACT. VACCINIUM MYRTILLUS FRUIT/LEAF EXTRACT. NARCISSUS POETICS CALLUS EXTRACT. ROSMARINUS OFFICINALIS (ROSEMARY) LEAF OIL, CITRUS RETICULATA (TANGERINE) PEEL OIL EUCALYPTUS GLOBULUS LEAF OIL. HYDROXYETHYLCELLULOSE. SODIUM CITRATE, CITRIC ACID. *Organic Ingredient

Questions or comments?

Call 1-877-902-2873